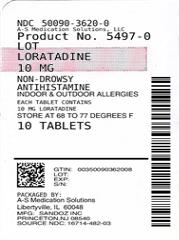 DRUG LABEL: Loratadine
NDC: 50090-3620 | Form: TABLET
Manufacturer: A-S Medication Solutions
Category: otc | Type: HUMAN OTC DRUG LABEL
Date: 20190429

ACTIVE INGREDIENTS: LORATADINE 10 mg/1 1
INACTIVE INGREDIENTS: LACTOSE MONOHYDRATE; MAGNESIUM STEARATE; MICROCRYSTALLINE CELLULOSE; SODIUM STARCH GLYCOLATE TYPE A POTATO

Drug Facts

Active Ingredient (in each tablet)

Loratadine, USP 10 mg

Purpose

Antihistamine

Uses

Temporarily relieves these symptoms due to hay fever or other upper respiratory allergies:

- runny nose
- itchy, watery eyes
- sneezing
- itching of the nose or throat

Warnings

Do not use

if you have ever had an allergic reaction to this product or any of its ingredients.

Ask a doctor before use if you have

liver or kidney disease.Your doctor should determine if you need a different dose.

When using this product

do not take more than directed. Taking more than directed may cause drowsiness.

Stop use and ask a doctor

if an allergic reaction to this product occurs. Seek medical help right away.

If pregnant or breast-feeding,

ask a health professional before use.

Keep out of reach of children.

In case of overdose, get medical help or contact a Poison Control Center right away.

Directions

adults and children 6 years and over | 1 tablet daily; not more than 1 tablet in 24 hours
children under 6 years of age | ask a doctor
consumers with liver or kidney disease | ask a doctor

Other Information

- Safety sealed: do not use if the imprinted bottle seal is open or torn (for bottle only).
- Safety sealed: do not use if open or torn (for blister package only).

STORAGE AND HANDLING

- Store at 20° to 25°C (68° to 77°F) (see USP Controlled Room Temperature).

Inactive Ingredients

Lactose monohydrate, magnesium stearate, microcrystalline cellulose and sodium starch glycolate.

Questions or comments?

1-800-206-7821

© 2005 NorthStar Healthcare Holdings I10-2015M

Manufactured for: Northstar Rx LLC

Memphis, TN 38141.

Manufactured by: Sandoz Inc.

Princeton, NJ 08540.

HOW SUPPLIED

Product: 50090-3620

NDC: 50090-3620-0 10 TABLET in a BOTTLE

NDC: 50090-3620-3 15 TABLET in a BOTTLE, PLASTIC

NDC: 50090-3620-4 30 TABLET in a BOTTLE, PLASTIC

NDC: 50090-3620-5 90 TABLET in a BOTTLE, PLASTIC

NDC: 50090-3620-1 20 TABLET in a BOTTLE, PLASTIC

NDC: 50090-3620-6 7 TABLET in a BOTTLE, PLASTIC